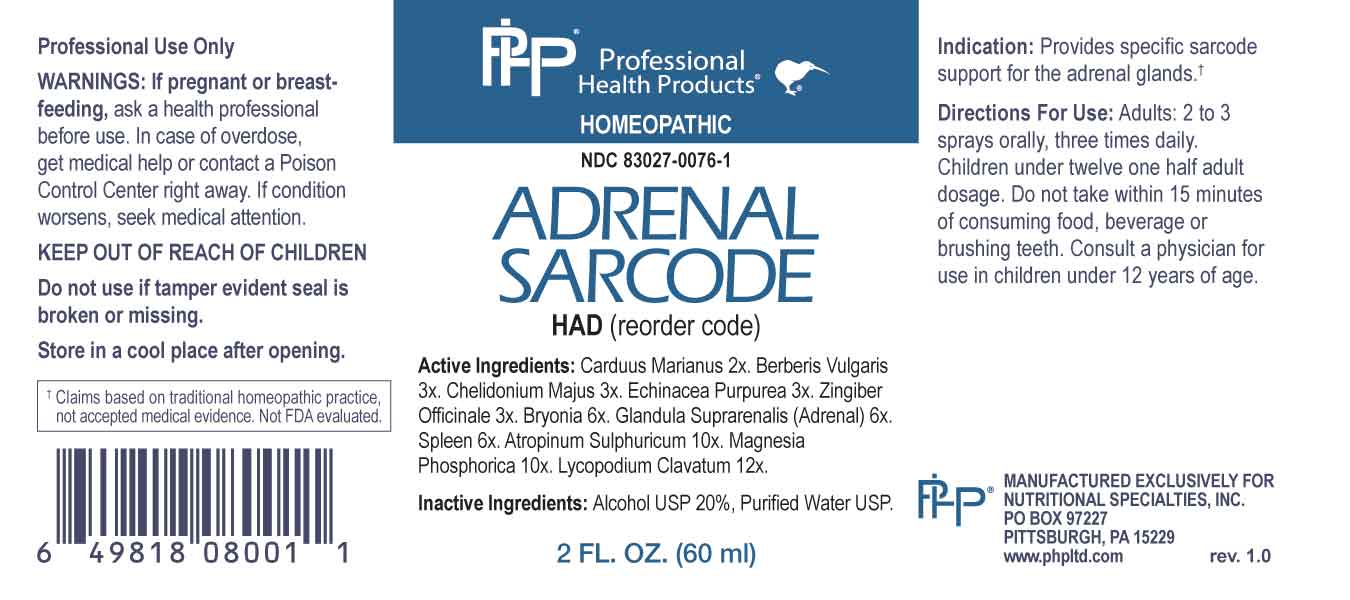 DRUG LABEL: Adrenal Sarcode
NDC: 83027-0076 | Form: SPRAY
Manufacturer: Nutritional Specialties, Inc.
Category: homeopathic | Type: HUMAN OTC DRUG LABEL
Date: 20230804

ACTIVE INGREDIENTS: MILK THISTLE 2 [hp_X]/1 mL; BERBERIS VULGARIS ROOT BARK 3 [hp_X]/1 mL; CHELIDONIUM MAJUS WHOLE 3 [hp_X]/1 mL; ECHINACEA PURPUREA WHOLE 3 [hp_X]/1 mL; GINGER 3 [hp_X]/1 mL; BRYONIA ALBA ROOT 6 [hp_X]/1 mL; BOS TAURUS ADRENAL GLAND 6 [hp_X]/1 mL; SUS SCROFA SPLEEN 6 [hp_X]/1 mL; ATROPINE SULFATE 10 [hp_X]/1 mL; MAGNESIUM PHOSPHATE, DIBASIC TRIHYDRATE 10 [hp_X]/1 mL; LYCOPODIUM CLAVATUM SPORE 12 [hp_X]/1 mL
INACTIVE INGREDIENTS: WATER; ALCOHOL

DRUG FACTS:

ACTIVE INGREDIENTS:

Carduus Marianus 2X, Berberis Vulgaris 3X, Chelidonium Majus 3X, Echinacea Purpurea 3X, Zingiber Officinale 3X, Bryonia 6X, Glandula Suprarenalis (Adrenal) 6X, Spleen 6X, Atropinum Sulphuricum 10X, Magnesia Phosphorica 10X, Lycopodium Clavatum 12X.

PURPOSE:

Provides specific sarcode support for the adrenal glands.

†Claims based on traditional homeopathic practice, not accepted medical evidence. Not FDA evaluated.

WARNINGS:

Professional Use Only

If pregnant or breast-feeding, ask a health professional before use.

In case of overdose, get medical help or contact a Poison Control Center right away.

If condition worsens, seek medical attention.

KEEP OUT OF REACH OF CHILDREN

Do not use if tamper evident seal is broken or missing.

Store in a cool place after opening

KEEP OUT OF REACH OF CHILDREN:

In case of overdose, get medical help or contact a Poison Control Center right away.

DIRECTIONS:

Adults: 2 to 3 sprays orally, three times daily. Children under twelve one half adult dosage. Do not take within 15 minutes of consuming food, beverage or brushing teeth. Consult a physician for use in children under 12 years of age.

INDICATIONS:

Provides specific sarcode support for the adrenal glands.†
†Claims based on traditional homeopathic practice, not accepted medical evidence. Not FDA evaluated.

INACTIVE INGREDIENTS:

Alcohol USP 20%, Purified Water USP.

QUESTIONS:

MANUFACTURED EXCLUSIVELY FOR

NUTRITIONAL SPECIALTIES, INC.

PO BOX 97227

PITTSBURG, PA 15229

www.phpltd.com

PACKAGE LABEL DISPLAY:

Professional

Health Products

HOMEOPATHIC

NDC 83027-0076-1

ADRENAL SARCODE

2 FL. OZ (60 ml)